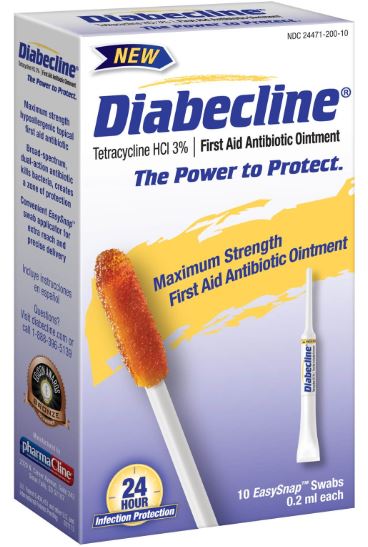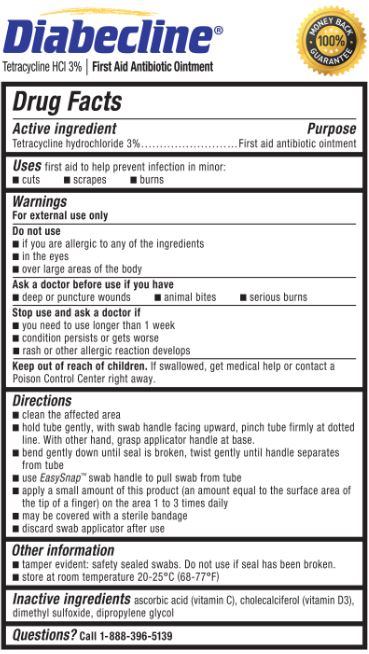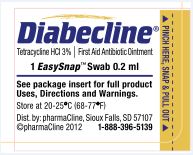 DRUG LABEL: Diabecline 
NDC: 24471-200 | Form: OINTMENT
Manufacturer: THRU PHARMA, LLC
Category: otc | Type: HUMAN OTC DRUG LABEL
Date: 20130523

ACTIVE INGREDIENTS: Tetracycline Hydrochloride 30 mg/1 mL
INACTIVE INGREDIENTS: Ascorbic Acid; Cholecalciferol; Dimethyl Sulfoxide; Dipropylene Glycol

Drug Facts

Active ingredient

Tetracycline hydrochloride 3%

Purpose

First aid antibiotic ointment

Uses

first aid to help prevent infection in minor:

- cuts
- scrapes
- burns

Warnings

For external use only

Do not use

- if you are allergic to any of the ingredients
- in the eyes
- over large areas of the body

Ask a doctor before use if you have

- deep or puncture wounds
- animal bites
- serious burns

Stop use and ask a doctor if

- you need to use longer than 1 week
- condition persists or gets worse
- rash or other allergic reaction develops

Keep out of reach of children.

If swallowed, get medical help or contact a Poison Control Center right away.

Directions

- clean the affected area
- hold the tube gently, with swab handle facing upward, pinch tube firmly at dotted line. With other hand, grasp applicator handle at base.
- bend gently down until seal is broken, twist gently until handle separates from tube
- use EasySnap™ handle to pull swab from tube
- apply a small amount of this product (an amount equal to the surface area of the tip of a finger) on the area 1 to 3 times daily
- may be covered with a sterile bandage
- discard swab applicator after use

Other information

- tamper evident: safety sealed swabs. Do not use if seal has been broken.
- store at room temperature 20-25°C (68-77°F)

Inactive ingredients

ascorbic acid (vitamin C), cholecalciferol (vitamin D3), dimethyl sulfoxide, dipropylene glycol

Questions?

Call 1-888-396-5139

Principal display panel

NEW! NDC 24471-200-10
Diabecline®
Tetracycline HCl 3% | First Aid Antibiotic Ointment
The Power to Protect.
Maximum Strength
First Aid Antibiotic Ointment
24 Hour Infection Protection
10 EasySnap™ Swabs
0.2 ml each

Maximum strength hypoallergenic topical first aid antibiotic
Broad-spectrum dual-action antibiotic kills bacteria, creates a zone of protection
Convenient EasySnap™ swab application for extra reach and precise delivery
Questions? Visit diabecline.com or call 1-888-396-5139
100% MONEY BACK GUARANTEE
PharmaCline

Diabecline®
Tetracycline HCl 3% | First Aid Antibiotic Ointment
100% MONEY BACK GUARANTEE

Diabecline®
Tetracycline HCl 3% | First Aid Antibiotic Ointment
with Vitamin D
1 EasySnap™ Swab 0.2 ml
See package insert for full product Uses, Directions and Warnings.
Store at 20-25°C (68-77°F)
Tamper evident: do not use if cap on swab is broken or missing
Dist. by: pharmaCline, Sioux Falls, SD 57107
©pharmaCline 2012 1-888-396-5139
PINCH HERE, SNAP & PULL OUT